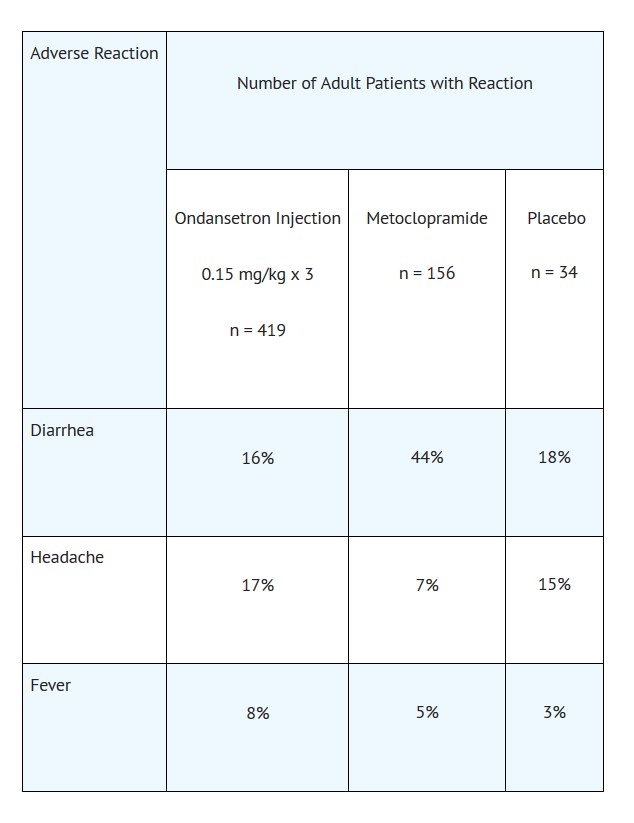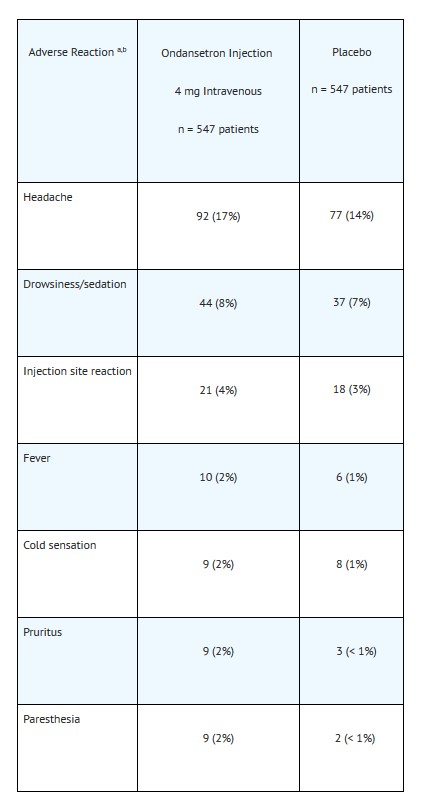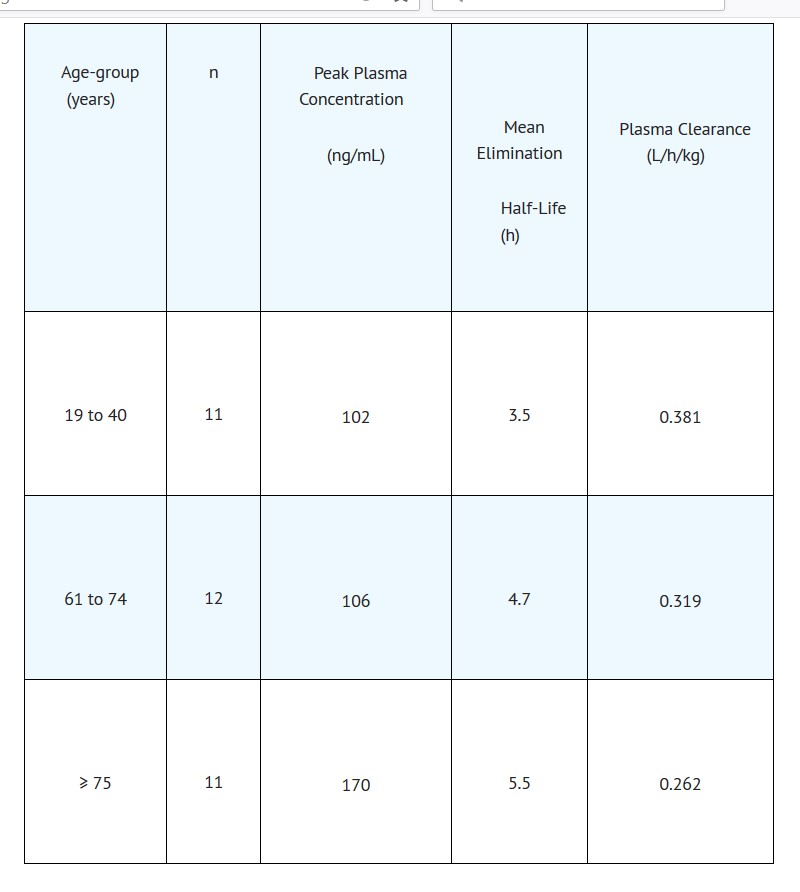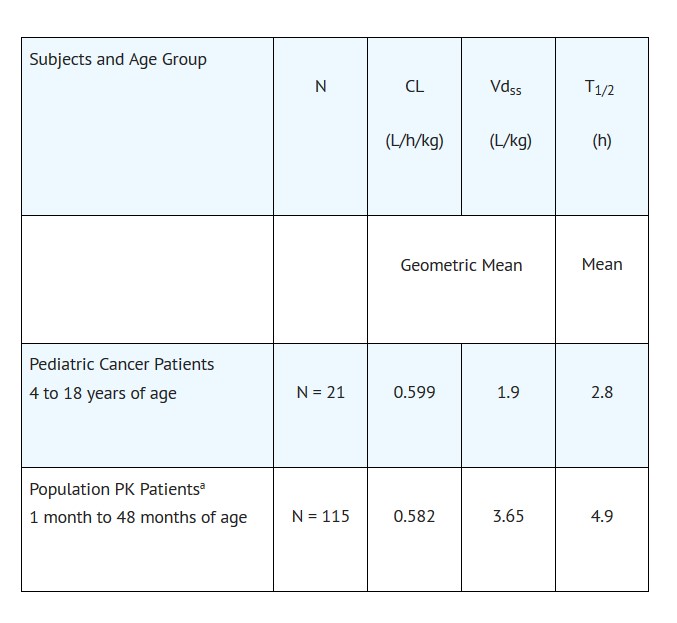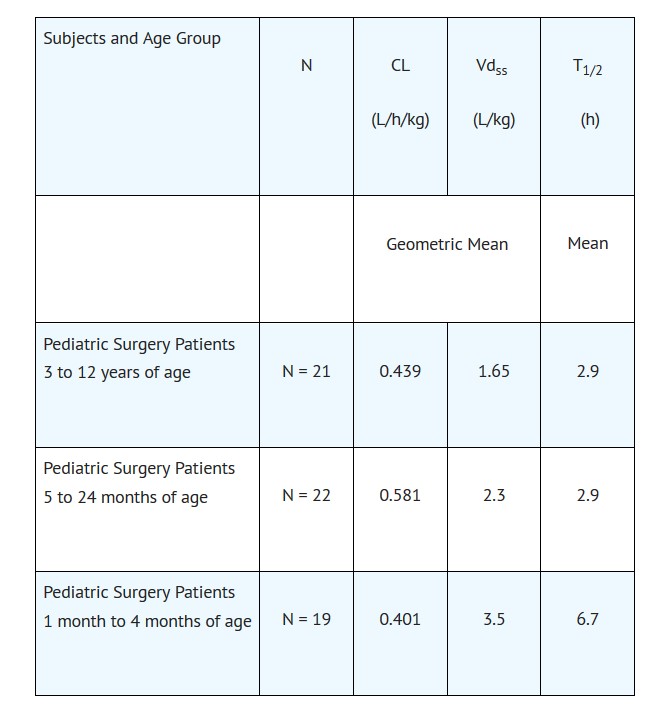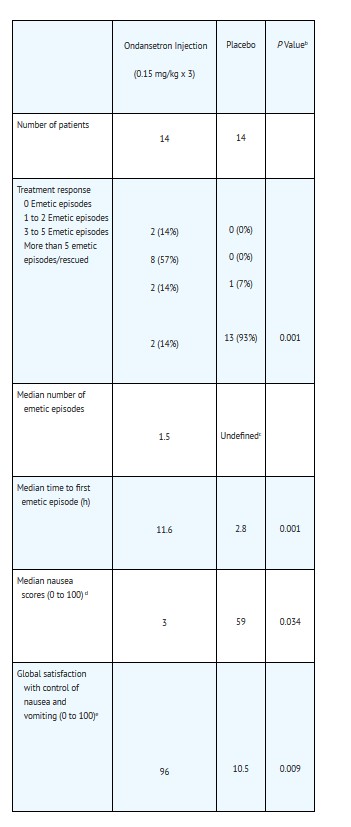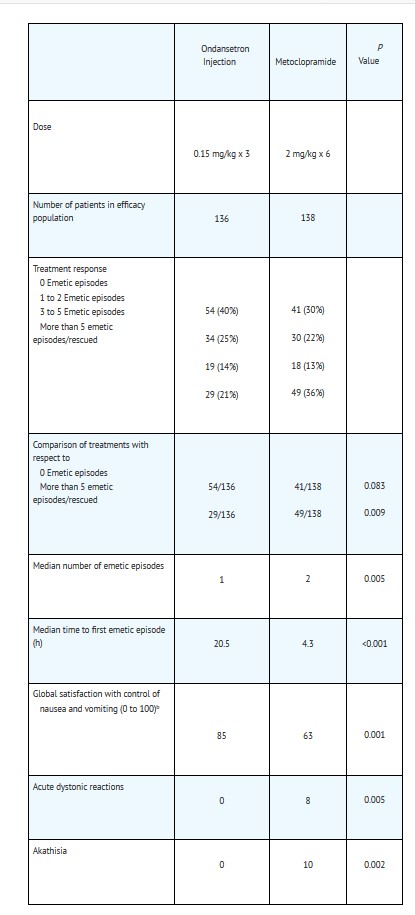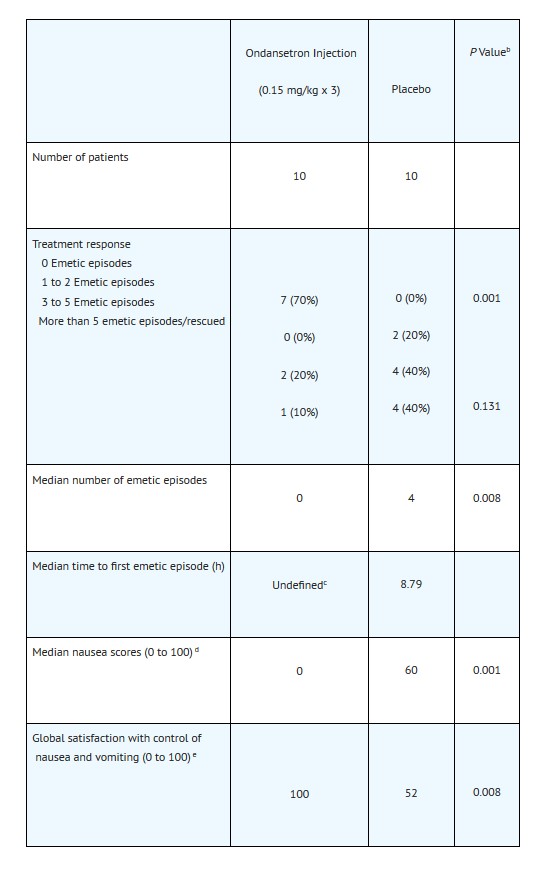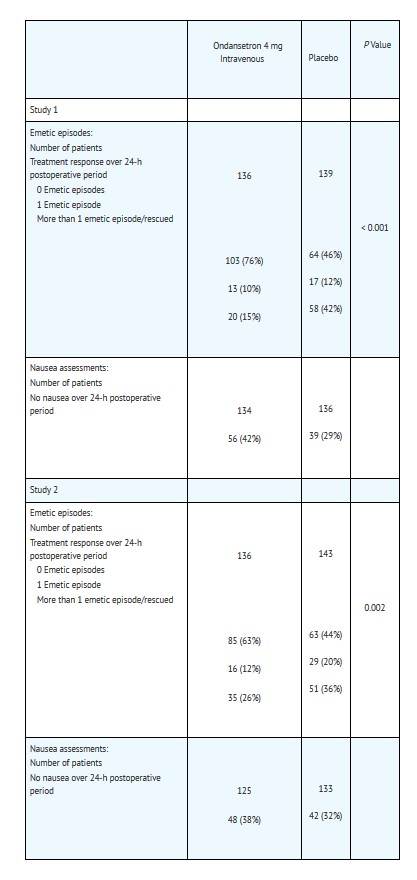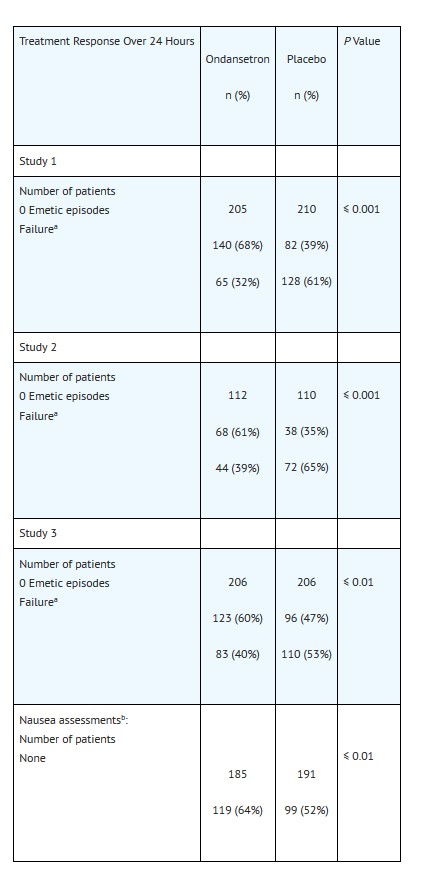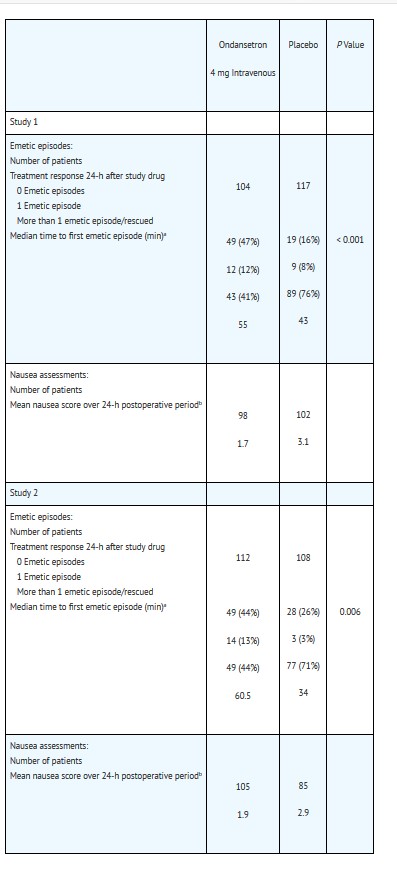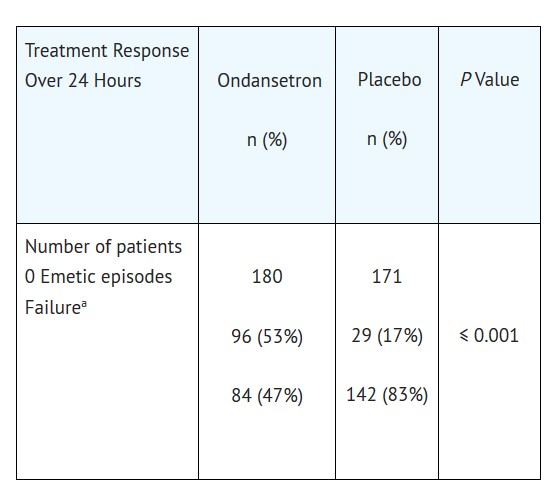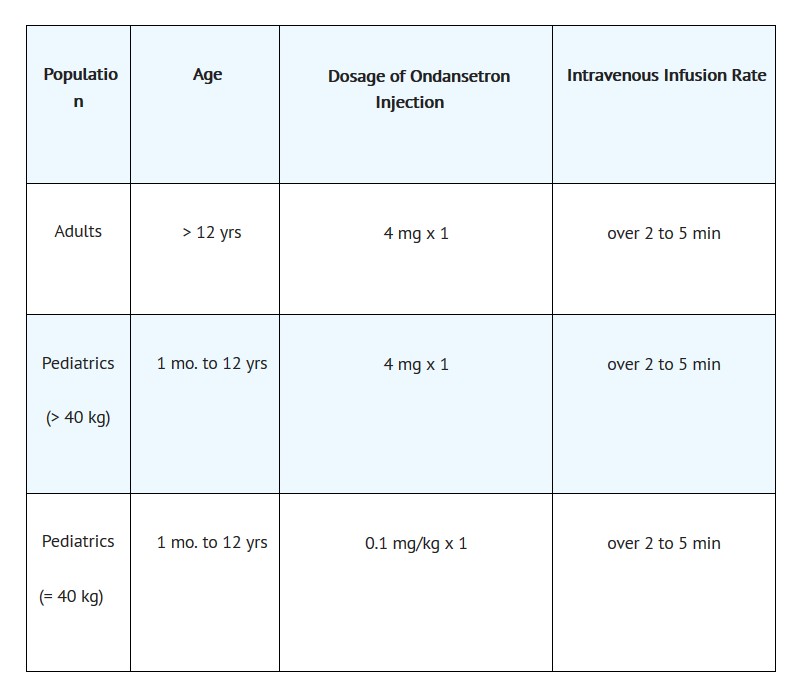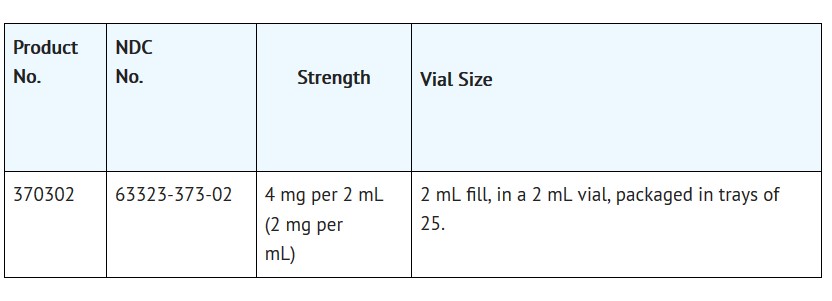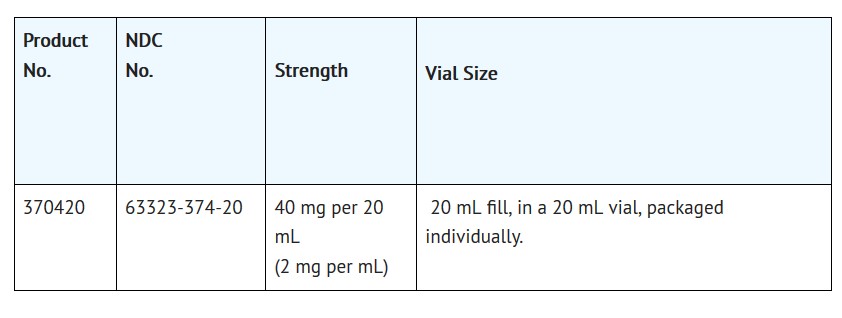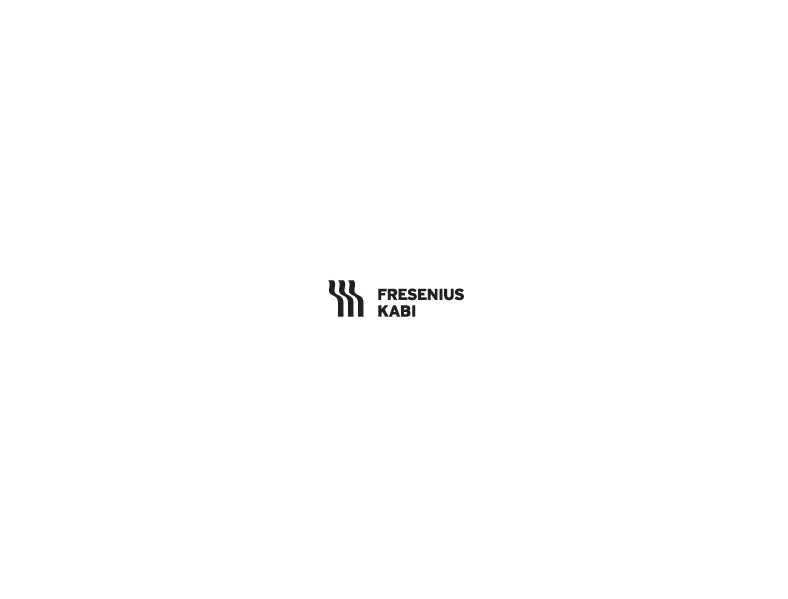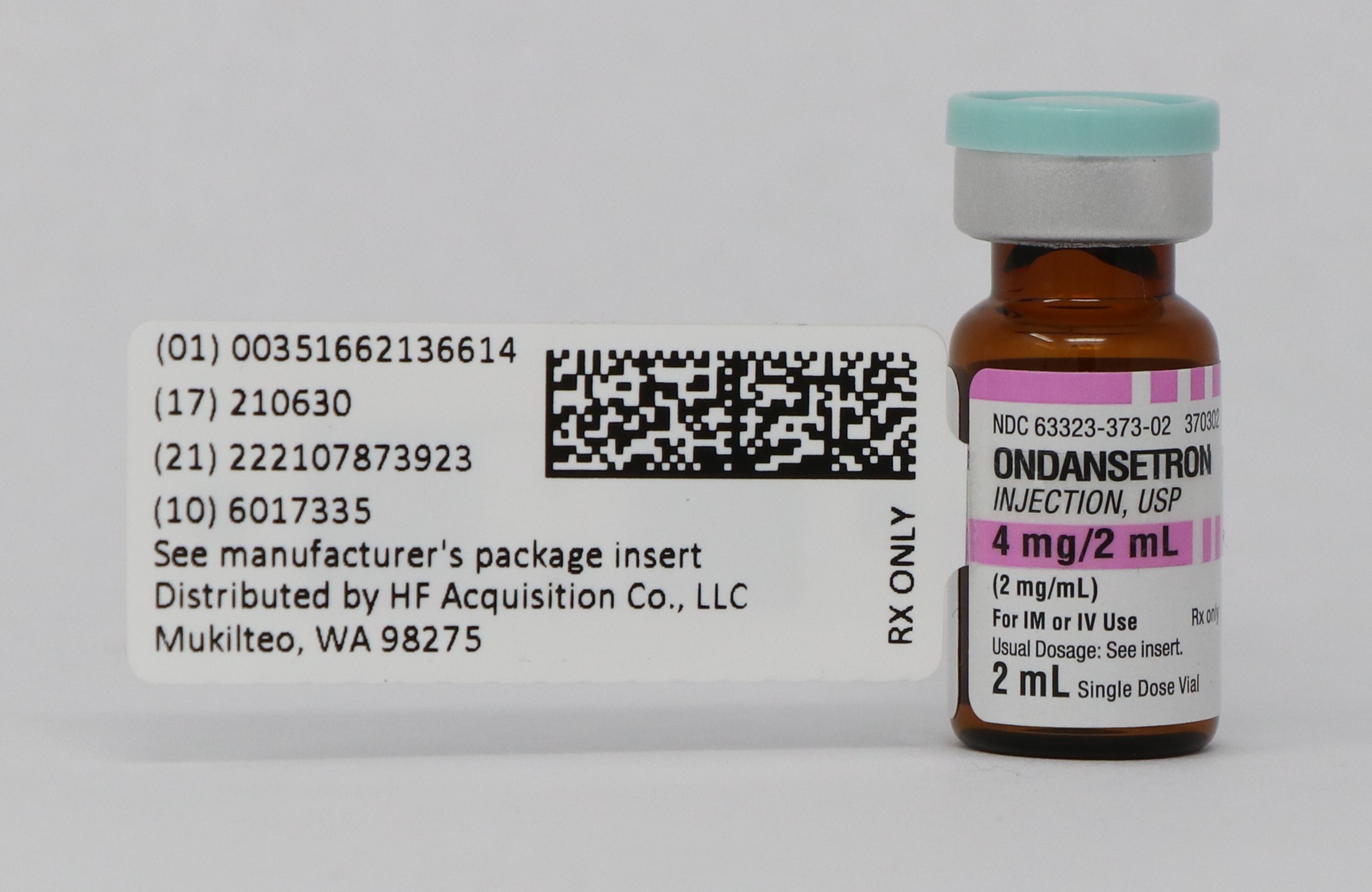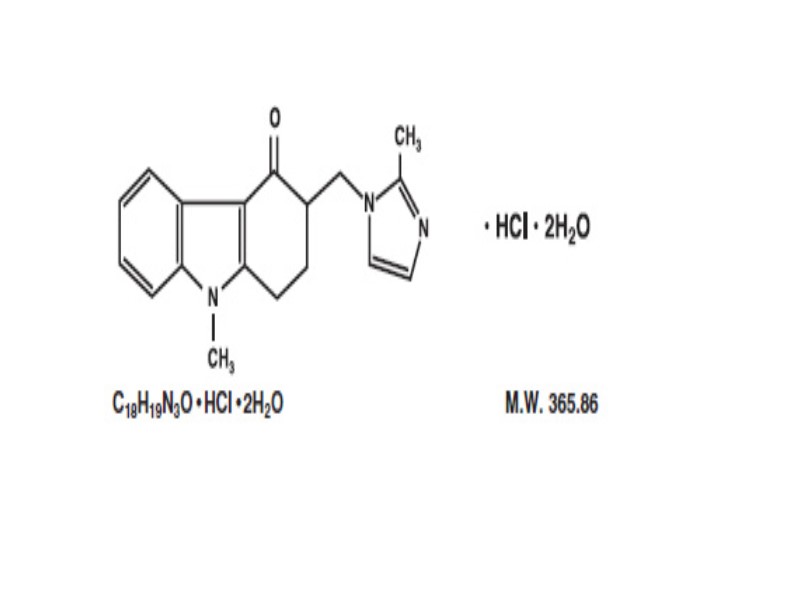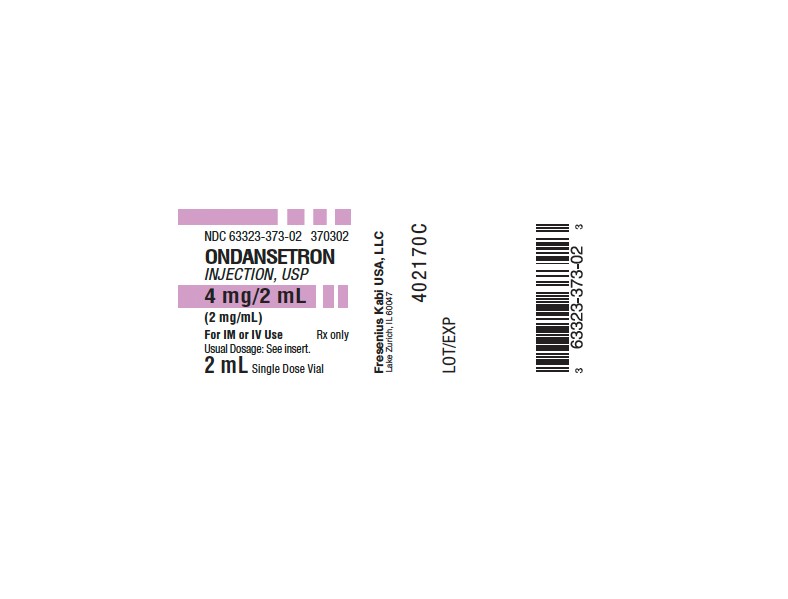 DRUG LABEL: ONDANSETRON
NDC: 51662-1366 | Form: INJECTION
Manufacturer: HF Acquisition Co LLC, DBA HealthFirst
Category: prescription | Type: HUMAN PRESCRIPTION DRUG LABEL
Date: 20221210

ACTIVE INGREDIENTS: ONDANSETRON HYDROCHLORIDE 2 mg/1 mL
INACTIVE INGREDIENTS: CITRIC ACID MONOHYDRATE 0.5 mg/1 mL; SODIUM CHLORIDE 9 mg/1 mL; SODIUM CITRATE 0.25 mg/1 mL

ONDANSETRON INJECTION, USP 4 mg/2 mL (2 mg/mL) 2 mL VIAL

HIGHLIGHTS OF PRESCRIBING INFORMATION

These highlights do not include all the information needed to use Ondansetron Injection, USP safely and effectively. See full prescribing information for Ondansetron Injection, USP.
ONDANSETRON injection, USP, for intravenous use
Initial U.S. Approval: 1991

RECENT MAJOR CHANGES

Warnings and Precautions, Serotonin Syndrome (5-5.3) 09/2014

INDICATIONS AND USAGE

Ondansetron Injection is a 5-HT3 receptor antagonist indicated:

Prevention of nausea and vomiting associated with initial and repeat courses of emetogenic cancer chemotherapy. (1-1.1)
Prevention of postoperative nausea and/or vomiting. (1-1.2)

DOSAGE AND ADMINISTRATION

Prevention of nausea and vomiting associated with initial and repeat courses of emetogenic cancer chemotherapy (2-2.1):

Adults and Pediatric patients (6 months to 18 years): Three 0.15 mg/kg doses, up to a maximum of 16 mg per dose, infused intravenously over 15 minutes. The first dose should be administered 30 minutes before the start of chemotherapy. Subsequent doses are administered 4 and 8 hours after the first dose.

Prevention of postoperative nausea and/or vomiting (2-2.2):

In patients with severe hepatic impairment, a total daily dose of 8 mg should not be exceeded. (2-2.4)

DOSAGE FORMS AND STRENGTHS

Ondansetron injection (2 mg per mL): 2 mL single use vials and 20 mL multiple dose vials. (3)

CONTRAINDICATIONS

Patients known to have hypersensitivity (e.g., anaphylaxis) to this product or any of its components. (4)
Concomitant use of apomorphine. (4)

WARNINGS AND PRECAUTIONS

Hypersensitivity reactions including anaphylaxis and bronchospasm, have been reported in patients who have exhibited hypersensitivity to other selective 5-HT3 receptor antagonists. (5-5.1)
QT prolongation occurs in a dose-dependent manner. Cases of Torsades de Pointes have been reported. Avoid ondansetron injection in patients with congenital long QT syndrome. (5-5.2)
Serotonin syndrome has been reported with 5-HT3 receptor antagonists alone but particularly with concomitant use of serotonergic drugs. (5-5.3)
Use in patients following abdominal surgery or in patients with chemotherapy-induced nausea and vomiting may mask a progressive ileus and/or gastric distention. (5-5.4, 5-5.5)

ADVERSE REACTIONS

Chemotherapy-Induced Nausea and Vomiting -

The most common adverse reactions (≥ 7%) in adults are diarrhea, headache, and fever. (6-6.1)

Postoperative Nausea and Vomiting -

The most common adverse reaction (≥ 10%) which occurs at a higher frequency compared to placebo in adults is headache. (6-6.1)
The most common adverse reaction (≥ 2%) which occurs at a higher frequency compared to placebo in pediatric patients 1 to 24 months of age is diarrhea. (6-6.1)

To report SUSPECTED ADVERSE REACTIONS, contact Fresenius Kabi Viglance & Medical Affairs at 1-800-551-7176 or FDA at 1-800-FDA-1088 or www.fda.gov/medwatch.

DRUG INTERACTIONS

Apomorphine – profound hypotension and loss of consciousness. Concomitant use with ondansetron is contraindicated. (7-7.2)

See 17 for PATIENT COUNSELING INFORMATION.

Revised: 6/2018

1 INDICATIONS & USAGE

1.1 Prevention of Nausea and Vomiting Associated with Initial and Repeat Courses of Emetogenic Cancer Chemotherapy

Ondansetron injection is indicated for the prevention of nausea and vomiting associated with initial and repeat courses of emetogenic cancer chemotherapy, including high-dose cisplatin [see CLINICAL STUDIES (14.1)].

Ondansetron is approved for patients aged 6 months and older.

1.2 Prevention of Postoperative Nausea and/or Vomiting

Ondansetron injection is indicated for the prevention of postoperative nausea and/or vomiting. As with other antiemetics, routine prophylaxis is not recommended for patients in whom there is little expectation that nausea and/or vomiting will occur postoperatively. In patients in whom nausea and/or vomiting must be avoided postoperatively, ondansetron injection is recommended even when the incidence of postoperative nausea and/or vomiting is low. For patients who do not receive prophylactic ondansetron injection and experience nausea and/or vomiting postoperatively, ondansetron injection may be given to prevent further episodes [see CLINICAL STUDIES (14.3)].

Ondansetron is approved for patients aged 1 month and older.

2 DOSAGE AND ADMINISTRATION

2.1 Prevention of Nausea and Vomiting Associated with Initial and Repeat Courses of Emetogenic Chemotherapy

Ondansetron injection should be diluted in 50 mL of 5% Dextrose Injection or 0.9% Sodium Chloride Injection before administration.

Adults:

The recommended adult intravenous dosage of ondansetron is three 0.15 mg/kg doses up to a maximum of 16 mg per dose [see CLINICAL PHARMACOLOGY (12.2)]. The first dose is infused over 15 minutes beginning 30 minutes before the start of emetogenic chemotherapy. Subsequent doses (0.15 mg/kg up to a maximum of 16 mg per dose) are administered 4 and 8 hours after the first dose of ondansetron.

Pediatrics:

For pediatric patients 6 months through 18 years of age, the intravenous dosage of ondansetron is three 0.15 mg/kg doses up to a maximum of 16 mg per dose [see CLINICAL STUDIES (14.1) and CLINICAL PHARMACOLOGY (12.2, 12.3)]. The first dose is to be administered 30 minutes before the start of moderately to highly emetogenic chemotherapy. Subsequent doses (0.15 mg/kg up to a maximum of 16 mg per dose) are administered 4 and 8 hours after the first dose of ondansetron. The drug should be infused intravenously over 15 minutes.

2.2 Prevention of Postoperative Nausea and Vomiting

Ondansetron injection should not be mixed with solutions for which physical and chemical compatibility have not been established. In particular, this applies to alkaline solutions as a precipitate may form.

Adults:

The recommended adult intravenous dosage of ondansetron is 4 mg undiluted administered intravenously in not less than 30 seconds, preferably over 2 to 5 minutes, immediately before induction of anesthesia, or postoperatively if the patient did not receive prophylactic antiemetics and experiences nausea and/or vomiting occurring within 2 hours after surgery. Alternatively, 4 mg undiluted may be administered intramuscularly as a single injection for adults. While recommended as a fixed dose for patients weighing more than 40 kg, few patients above 80 kg have been studied. In patients who do not achieve adequate control of postoperative nausea and vomiting following a single, prophylactic, preinduction, intravenous dose of ondansetron 4 mg, administration of a second intravenous dose of 4 mg ondansetron postoperatively does not provide additional control of nausea and vomiting.

Pediatrics:

For pediatric patients 1 month through 12 years of age, the dosage is a single 0.1 mg/kg dose for patients weighing 40 kg or less, or a single 4 mg dose for patients weighing more than 40 kg. The rate of administration should not be less than 30 seconds, preferably over 2 to 5 minutes immediately prior to or following anesthesia induction, or postoperatively if the patient did not receive prophylactic antiemetics and experiences nausea and/or vomiting occurring shortly after surgery. Prevention of further nausea and vomiting was only studied in patients who had not received prophylactic ondansetron.

2.3 Stability and Handling

After dilution, do not use beyond 24 hours. Although ondansetron injection is chemically and physically stable when diluted as recommended, sterile precautions should be observed because diluents generally do not contain preservative.

Ondansetron injection is stable at room temperature under normal lighting conditions for 48 hours after dilution with the following intravenous fluids: 0.9% Sodium Chloride Injection, 5% Dextrose Injection, 5% Dextrose and 0.9% Sodium Chloride Injection, 5% Dextrose and 0.45% Sodium Chloride Injection, and 3% Sodium Chloride Injection.

Note: Parenteral drug products should be inspected visually for particulate matter and discoloration before administration whenever solution and container permit.

Precaution: Occasionally, ondansetron precipitates at the stopper/vial interface in vials stored upright. Potency and safety are not affected. If a precipitate is observed, resolubilize by shaking the vial vigorously.

2.4 Dosage Adjustment for Patients with Impaired Hepatic Function

In patients with severe hepatic impairment (Child-Pugh score of 10 or greater), a single maximal daily dose of 8 mg infused over 15 minutes beginning 30 minutes before the start of the emetogenic chemotherapy is recommended. There is no experience beyond first-day administration of ondansetron in these patients [see CLINICAL PHARMACOLOGY (12.3)].

3 DOSAGE FORMS & STRENGTHS

Ondansetron injection, 2 mg per mL is a clear, colorless, nonpyrogenic, sterile solution available as a 2 mL single use vial and a 20 mL multiple dose vial.

4 CONTRAINDICATIONS

Ondansetron injection is contraindicated for patients known to have hypersensitivity (e.g., anaphylaxis) to this product or any of its components. Anaphylactic reactions have been reported in patients taking ondansetron [see ADVERSE REACTIONS (6.2)].

The concomitant use of apomorphine with ondansetron is contraindicated based on reports of profound hypotension and loss of consciousness when apomorphine was administered with ondansetron.

5 WARNINGS AND PRECAUTIONS

5.1 Hypersensitivity Reactions

Hypersensitivity reactions, including anaphylaxis and bronchospasm, have been reported in patients who have exhibited hypersensitivity to other selective 5-HT3 receptor antagonists.

5.2 QT Prolongation

Ondansetron prolongs the QT interval in a dose-dependent manner [see CLINICAL PHARMACOLOGY (12.2)]. In addition, postmarketing cases of Torsades de Pointes have been reported in patients using ondansetron. Avoid ondansetron in patients with congenital long QT syndrome. ECG monitoring is recommended in patients with electrolyte abnormalities (e.g., hypokalemia or hypomagnesemia), congestive heart failure, bradyarrhythmias, or patients taking other medicinal products that lead to QT prolongation.

5.3 Serotonin Syndrome

The development of serotonin syndrome has been reported with 5-HT3 receptor antagonists. Most reports have been associated with concomitant use of serotonergic drugs (e.g., selective serotonin reuptake inhibitors (SSRIs), serotonin and norepinephrine reuptake inhibitors (SNRIs), monoamine oxidase inhibitors, mirtazapine, fentanyl, lithium, tramadol, and intravenous methylene blue). Some of the reported cases were fatal. Serotonin syndrome occurring with overdose of ondansetron alone has also been reported. The majority of reports of serotonin syndrome related to 5-HT3 receptor antagonist use occurred in a post-anesthesia care unit or an infusion center.

Symptoms associated with serotonin syndrome may include the following combination of signs and symptoms: mental status changes (e.g., agitation, hallucinations, delirium, and coma), autonomic instability (e.g., tachycardia, labile blood pressure, dizziness, diaphoresis, flushing, hyperthermia), neuromuscular symptoms (e.g., tremor, rigidity, myoclonus, hyperreflexia, incoordination), seizures, with or without gastrointestinal symptoms (e.g., nausea, vomiting, diarrhea). Patients should be monitored for the emergence of serotonin syndrome, especially with concomitant use of ondansetron and other serotonergic drugs. If symptoms of serotonin syndrome occur, discontinue ondansetron and initiate supportive treatment. Patients should be informed of the increased risk of serotonin syndrome, especially if ondansetron is used concomitantly with other serotonergic drugs [see DRUG INTERACTIONS (7.5), OVERDOSAGE (10) and PATIENT COUNSELING INFORMATION (17)].

5.4 Masking of Progressive Ileus and Gastric Distension

The use of ondansetron in patients following abdominal surgery or in patients with chemotherapy-induced nausea and vomiting may mask a progressive ileus and gastric distention.

5.5 Effect on Peristalsis

Ondansetron is not a drug that stimulates gastric or intestinal peristalsis. It should not be used instead of nasogastric suction.

6 ADVERSE REACTIONS

6.1 Clinical Trials Experience

Because clinical trials are conducted under widely varying conditions, adverse reaction rates observed in the clinical trials of a drug cannot be directly compared to rates in the clinical trials of another drug and may not reflect the rates observed in clinical practice.

The following adverse reactions have been reported in clinical trials of adult patients treated with ondansetron, the active ingredient of intravenous ondansetron across a range of dosages. A causal relationship to therapy with ondansetron was unclear in many cases.

Chemotherapy-Induced Nausea and Vomiting:

Table 1: Adverse Reactions Reported in > 5% of Adult Patients Who

Received Ondansetron at a Dosage of Three 0.15 mg/kg Doses

Cardiovascular: Rare cases of angina (chest pain), electrocardiographic alterations, hypotension, and tachycardia have been reported.
Gastrointestinal: Constipation has been reported in 11% of chemotherapy patients receiving multiday ondansetron.
Hepatic: In comparative trials in cisplatin chemotherapy patients with normal baseline values of aspartate transaminase (AST) and alanine transaminase (ALT), these enzymes have been reported to exceed twice the upper limit of normal in approximately 5% of patients. The increases were transient and did not appear to be related to dose or duration of therapy. On repeat exposure, similar transient elevations in transaminase values occurred in some courses, but symptomatic hepatic disease did not occur.
Integumentary: Rash has occurred in approximately 1% of patients receiving ondansetron.
Neurological: There have been rare reports consistent with, but not diagnostic of, extrapyramidal reactions in patients receiving ondansetron injection, and rare cases of grand mal seizure.
Other: Rare cases of hypokalemia have been reported.
Postoperative Nausea and Vomiting:

The adverse reactions in Table 2 have been reported in ≥ 2% of adults receiving ondansetron at a dosage of 4 mg intravenous over 2 to 5 minutes in clinical trials.

Table 2: Adverse Reactions Reported in ≥ 2% (and with Greater

Frequency than the Placebo Group) of Adult Patients Receiving

Ondansetron at a Dosage of 4 mg Intravenous over 2 to 5 Minutes

a Adverse Reactions: Rates of these reactions were not significantly different in the ondansetron and placebo groups

b Patients were receiving multiple concomitant perioperative and postoperative medications

Pediatric Use:
Rates of adverse reactions were similar in both the ondansetron and placebo groups in pediatric patients receiving ondansetron (a single 0.1 mg/kg dose for pediatric patients weighing 40 kg or less, or 4 mg for pediatric patients weighing more than 40 kg) administered intravenously over at least 30 seconds. Diarrhea was seen more frequently in patients taking ondansetron (2%) compared to placebo (< 1%) in the 1 month to 24 month age group. These patients were receiving multiple concomitant perioperative and postoperative medications.

6.2 Postmarketing Experience

The following adverse reactions have been identified during post-approval use of ondansetron. Because these reactions are reported voluntarily from a population of uncertain size, it is not always possible to reliably estimate their frequency or establish a causal relationship to drug exposure. The reactions have been chosen for inclusion due to a combination of their seriousness, frequency of reporting, or potential causal connection to ondansetron.

Cardiovascular: Arrhythmias (including ventricular and supraventricular tachycardia, premature ventricular contractions, and atrial fibrillation), bradycardia, electrocardiographic alterations (including second-degree heart block, QT/QTc interval prolongation, and ST segment depression), palpitations, and syncope. Rarely and predominantly with intravenous ondansetron, transient ECG changes including QT/QTc interval prolongation have been reported [see WARNINGS AND PRECAUTIONS (5.2)].

General: Flushing. Rare cases of hypersensitivity reactions, sometimes severe (e.g., anaphylactic reactions, angioedema, bronchospasm, cardiopulmonary arrest, hypotension, laryngeal edema, laryngospasm, shock, shortness of breath, stridor) have also been reported. A positive lymphocyte transformation test to ondansetron has been reported, which suggests immunologic sensitivity to ondansetron.

Hepatobiliary: Liver enzyme abnormalities have been reported. Liver failure and death have been reported in patients with cancer receiving concurrent medications including potentially hepatotoxic cytotoxic chemotherapy and antibiotics.

Local Reactions: Pain, redness, and burning at site of injection.

Lower Respiratory: Hiccups.

Neurological: Oculogyric crisis, appearing alone, as well as with other dystonic reactions. Transient dizziness during or shortly after intravenous infusion.

Skin: Urticaria, Stevens-Johnson syndrome, and toxic epidermal necrolysis.

Eye Disorders: Cases of transient blindness, predominantly during intravenous administration, have been reported. These cases of transient blindness were reported to resolve within a few minutes up to 48 hours. Transient blurred vision, in some cases associated with abnormalities of accommodation, have also been reported.

7 DRUG INTERACTIONS

7.1 Drugs Affecting Cytochrome P-450 Enzymes

Ondansetron does not appear to induce or inhibit the cytochrome P-450 drug-metabolizing enzyme system of the liver. Because ondansetron is metabolized by hepatic cytochrome P-450 drug-metabolizing enzymes (CYP3A4, CYP2D6, CYP1A2), inducers or inhibitors of these enzymes may change the clearance and, hence, the half-life of ondansetron [see CLINICAL PHARMACOLOGY (12.3)]. On the basis of limited available data, no dosage adjustment is recommended for patients on these drugs.

7.2 Apomorphine

Based on reports of profound hypotension and loss of consciousness when apomorphine was administered with ondansetron, the concomitant use of apomorphine with ondansetron is contraindicated [see CONTRAINDICATIONS (4)].

7.3 Phenytoin, Carbamazepine, and Rifampin

In patients treated with potent inducers of CYP3A4 (i.e., phenytoin, carbamazepine, and rifampin), the clearance of ondansetron was significantly increased and ondansetron blood concentrations were decreased. However, on the basis of available data, no dosage adjustment for ondansetron is recommended for patients on these drugs [see CLINICAL PHARMACOLOGY (12.3)].

7.4 Tramadol

Although there are no data on pharmacokinetic drug interactions between ondansetron and tramadol, data from two small studies indicate that concomitant use of ondansetron may result in reduced analgesic activity of tramadol. Patients on concomitant ondansetron self administered tramadol more frequently in these studies, leading to an increased cumulative dose in patient controlled administration (PCA) of tramadol.

7.5 Serotonergic Drugs

Serotinin syndrome (including altered mental status, autonomic instability, and neuromuscular symptoms) has been described following the concomitant use of 5-HT3 receptor antagonists and other serotonergic drugs, including selective serotonin reuptake inhibitors (SSRIs) and serotonin and noradrenaline reuptake inhibitors (SNRIs) [see WARNINGS AND PRECAUTIONS (5.3)].

7.6 Chemotherapy

In humans, carmustine, etoposide, and cisplatin do not affect the pharmacokinetics of ondansetron.

In a crossover study in 76 pediatric patients, intravenous ondansetron did not increase blood levels of high-dose methotrexate.

7.7 Temazepam

The coadministration of ondansetron had no effect on the pharmacokinetics and pharmacodynamics of temazepam.

7.8 Alfentanil and Atracurium

Ondansetron does not alter the respiratory depressant effects produced by alfentanil or the degree of neuromuscular blockade produced by atracurium. Interactions with general or local anesthetics have not been studied.

8 USE IN SPECIFIC POPULATIONS

8.1 Pregnancy

Pregnancy Category B. Reproduction studies have been performed in pregnant rats and rabbits at intravenous doses up to 4 mg/kg per day (approximately 1.4 and 2.9 times the recommended human intravenous dose of 0.15 mg/kg given three times a day, respectively, based on body surface area) and have revealed no evidence of impaired fertility or harm to the fetus due to ondansetron. There are, however, no adequate and well-controlled studies in pregnant women. Because animal reproduction studies are not always predictive of human response, this drug should be used during pregnancy only if clearly needed.

8.3 Nursing Mothers

Ondansetron is excreted in the breast milk of rats. It is not known whether ondansetron is excreted in human milk. Because many drugs are excreted in human milk, caution should be exercised when ondansetron is administered to a nursing woman.

8.4 Pediatric Use

Little information is available about the use of ondansetron in pediatric surgical patients younger than 1 month of age [see CLINICAL STUDIES (14.2)]. Little information is available about the use of ondansetron in pediatric cancer patients younger than 6 months of age [see CLINICAL STUDIES (14.1) and DOSAGE & ADMINISTRATION (2)].

The clearance of ondansetron in pediatric patients 1 month to 4 months of age is slower and the half-life is ~2.5 fold longer than patients who are > 4 to 24 months of age. As a precaution, it is recommended that patients less than 4 months of age receiving this drug be closely monitored [see CLINICAL PHARMACOLOGY (12.3)].

8.5 Geriatric Use

Of the total number of subjects enrolled in cancer chemotherapy-induced and postoperative nausea and vomiting in US- and foreign-controlled clinical trials, 862 were 65 years of age and over. No overall differences in safety or effectiveness were observed between these subjects and younger subjects, and other reported clinical experience has not identified differences in responses between the elderly and younger patients, but greater sensitivity of some older individuals cannot be ruled out. Dosage adjustment is not needed in patients over the age of 65 [see CLINICAL PHARMACOLOGY (12.3)].

8.6 Hepatic Impairment

In patients with severe hepatic impairment (Child-Pugh score of 10 or greater), clearance is reduced and apparent volume of distribution is increased with a resultant increase in plasma half-life [see CLINICAL PHARMACOLOGY (12.3)]. In such patients, a total daily dose of 8 mg should not be exceeded [see DOSAGE & ADMINISTRATION (2.3)].

8.7 Renal Impairment

Although plasma clearance is reduced in patients with severe renal impairment (creatinine clearance < 30 mL/min), no dosage adjustment is recommended [see CLINICAL PHARMACOLOGY (12.3)].

9 DRUG ABUSE AND DEPENDENCE

Animal studies have shown that ondansetron is not discriminated as a benzodiazepine nor does it substitute for benzodiazepines in direct addiction studies.

10 OVERDOSAGE

There is no specific antidote for ondansetron overdose. Patients should be managed with appropriate supportive therapy. Individual intravenous doses as large as 150 mg and total daily intravenous doses as large as 252 mg have been inadvertently administered without significant adverse events. These doses are more than 10 times the recommended daily dose.

In addition to the adverse reactions listed above, the following events have been described in the setting of ondansetron overdose: “Sudden blindness” (amaurosis) of 2 to 3 minutes’ duration plus severe constipation occurred in one patient that was administered 72 mg of ondansetron intravenously as a single dose. Hypotension (and faintness) occurred in another patient that took 48 mg of oral ondansetron. Following infusion of 32 mg over only a 4-minute period, a vasovagal episode with transient second-degree heart block was observed. In all instances, the events resolved completely.

Pediatric cases consistent with serotonin syndrome have been reported after inadvertent oral overdoses of ondansetron (exceeding estimated ingestion of 5 mg/kg) in young children. Reported symptoms included somnolence, agitation, tachycardia, tachypnea, hypertension, flushing, mydriasis, diaphoresis, myoclonic movements, horizontal nystagmus, hyperreflexia, and seizure. Patients required supportive care, including intubation in some cases, with complete recovery without sequelae within 1 to 2 days.

11 DESCRIPTION

The active ingredient of Ondansetron Injection, USP is ondansetron hydrochloride, the racemic form of ondansetron and a selective blocking agent of the serotonin 5-HT3 receptor type. Chemically it is (±) 1, 2, 3, 9-tetrahydro-9-methyl-3-[(2-methyl-1H-imidazol-1-yl)methyl]-4H-carbazol-4-one, monohydrochloride dihydrate. It has the following structural formula:

Ondansetron is a white to off-white powder that is sparingly soluble in water.
Each mL of the preservative-free aqueous solution in the 2 mL single use vial contains 2 mg of ondansetron as the hydrochloride; 9 mg of sodium chloride; and 0.5 mg of citric acid monohydrate and 0.25 mg of sodium citrate dihydrate as buffers in water for injection.
Each mL of the preserved aqueous solution in the 20 mL multiple dose vial contains 2 mg of ondansetron as the hydrochloride; 8.3 mg of sodium chloride; 0.5 mg of citric acid monohydrate and 0.25 mg of sodium citrate dihydrate as buffers; and 1.2 mg of methylparaben and 0.15 mg of propylparaben as preservatives in water for injection.
Ondansetron Injection is a clear, colorless, nonpyrogenic, sterile solution for intravenous use. The pH of the injection solution is 3.3 to 4.0.

12 CLINICAL PHARMACOLOGY

12.1 Mechanism of Action

Ondansetron is a selective 5-HT3 receptor antagonist. While ondansetron’s mechanism of action has not been fully characterized, it is not a dopamine-receptor antagonist.

12.2 Pharmacodynamics

QTc interval prolongation was studied in a double blind, single intravenous dose, placebo- and positive-controlled, crossover study in 58 healthy subjects. The maximum mean (95% upper confidence bound) difference in QTcF from placebo after baseline-correction was 19.5 (21.8) ms and 5.6 (7.4) ms after 15 minute intravenous infusions of 32 mg and 8 mg ondansetron, respectively. A significant exposure-response relationship was identified between ondansetron concentration and ΔΔQTcF. Using the established exposure-response relationship, 24 mg infused intravenously over 15 min had a mean predicted (95% upper prediction interval) ΔΔQTcF of 14 (16.3) ms. In contrast, 16 mg infused intravenously over 15 min using the same model had a mean predicted (95% upper prediction interval) ΔΔQTcF of 9.1 (11.2) ms.

In normal volunteers, single intravenous doses of 0.15 mg/kg of ondansetron had no effect on esophageal motility, gastric motility, lower esophageal sphincter pressure, or small intestinal transit time. In another study in six normal male volunteers, a 16 mg dose infused over 5 minutes showed no effect of the drug on cardiac output, heart rate, stroke volume, blood pressure, or electrocardiogram (ECG). Multiday administration of ondansetron has been shown to slow colonic transit in normal volunteers. Ondansetron has no effect on plasma prolactin concentrations. In a gender-balanced pharmacodynamic study (n = 56), ondansetron 4 mg administered intravenously or intramuscularly was dynamically similar in the prevention of nausea and vomiting using the ipecacuanha model of emesis.

12.3 Pharmacokinetics

In normal adult volunteers, the following mean pharmacokinetic data have been determined following a single 0.15 mg/kg intravenous dose.

Table 3: Pharmacokinetics in Normal Adult Volunteers

Absorption: A study was performed in normal volunteers (n = 56) to evaluate the pharmacokinetics of a single 4 mg dose administered as a 5 minute infusion compared to a single intramuscular injection. Systemic exposure as measured by mean AUC were equivalent, with values of 156 [95% CI 136, 180] and 161 [95% CI 137, 190] ng•h/mL for intravenous and intramuscular groups, respectively. Mean peak plasma concentrations were 42.9 [95% CI 33.8, 54.4] ng/mL at 10 minutes after intravenous infusion and 31.9 [95% CI 26.3, 38.6] ng/mL at 41 minutes after intramuscular injection.
Distribution: Plasma protein binding of ondansetron as measured in vitro was 70% to 76%, over the pharmacologic concentration range of 10 to 500 ng/mL. Circulating drug also distributes into erythrocytes.
Metabolism: Ondansetron is extensively metabolized in humans, with approximately 5% of a radiolabeled dose recovered as the parent compound from the urine. The primary metabolic pathway is hydroxylation on the indole ring followed by subsequent glucuronide or sulfate conjugation.
Although some nonconjugated metabolites have pharmacologic activity, these are not found in plasma at concentrations likely to significantly contribute to the biological activity of ondansetron. The metabolites are observed in the urine.
In vitro metabolism studies have shown that ondansetron is a substrate for multiple human hepatic cytochrome P-450 enzymes, including CYP1A2, CYP2D6, and CYP3A4. In terms of overall ondansetron turnover, CYP3A4 plays a predominant role while formation of the major in vivo metabolites is apparently mediated by CYP1A2. The role of CYP2D6 in ondansetron in vivo metabolism is relatively minor.
The pharmacokinetics of intravenous ondansetron did not differ between subjects who were poor metabolizers of CYP2D6 and those who were extensive metabolizers of CYP2D6, further supporting the limited role of CYP2D6 in ondansetron disposition in vivo.
Elimination: In adult cancer patients, the mean ondansetron elimination half-life was 4 hours, and there was no difference in the multiple dose pharmacokinetics over a 4 day period. In a dose proportionality study, systemic exposure to 32 mg of ondansetron was not proportional to dose as measured by comparing dose-normalized AUC values to an 8 mg dose. This is consistent with a small decrease in systemic clearance with increasing plasma concentrations.

Geriatrics: A reduction in clearance and increase in elimination half-life are seen in patients over 75 years of age. In clinical trials with cancer patients, safety and efficacy were similar in patients over 65 years of age and those under 65 years of age; there was an insufficient number of patients over 75 years of age to permit conclusions in that age-group. No dosage adjustment is recommended in the elderly.
Pediatrics: Pharmacokinetic samples were collected from 74 cancer patients 6 to 48 months of age, who received a dose of 0.15 mg/kg of intravenous ondansetron every 4 hours for 3 doses during a safety and efficacy trial. These data were combined with sequential pharmacokinetics data from 41 surgery patients 1 month to 24 months of age, who received a single dose of 0.1 mg/kg of intravenous ondansetron prior to surgery with general anesthesia, and a population pharmacokinetic analysis was performed on the combined data set. The results of this analysis are included in Table 4 and are compared to the pharmacokinetic results in cancer patients 4 to 18 years of age.

Table 4: Pharmacokinetics in Pediatric Cancer Patients

1 Month to 18 Years of Age

a Population PK (Pharmacokinetic) Patients: 64% cancer patients and 36% surgery patients.

Based on the population pharmacokinetic analysis, cancer patients 6 to 48 months of age who receive a dose of 0.15 mg/kg of intravenous ondansetron every 4 hours for 3 doses would be expected to achieve a systemic exposure (AUC) consistent with the exposure achieved in previous pediatric studies in cancer patients (4 to 18 years of age) at similar doses.
In a study of 21 pediatric patients (3 to 12 years of age) who were undergoing surgery requiring anesthesia for a duration of 45 minutes to 2 hours, a single intravenous dose of ondansetron, 2 mg (3 to 7 years) or 4 mg (8 to 12 years), was administered immediately prior to anesthesia induction. Mean weight-normalized clearance and volume of distribution values in these pediatric surgical patients were similar to those previously reported for young adults. Mean terminal half-life was slightly reduced in pediatric patients (range, 2.5 to 3 hours) in comparison with adults (range, 3 to 3.5 hours).
In a study of 51 pediatric patients (1 month to 24 months of age) who were undergoing surgery requiring general anesthesia, a single intravenous dose of ondansetron, 0.1 or 0.2 mg/kg, was administered prior to surgery. As shown in Table 5, the 41 patients with pharmacokinetic data were divided into 2 groups, patients 1 month to 4 months of age and patients 5 to 24 months of age, and are compared to pediatric patients 3 to 12 years of age.

Table 5: Pharmacokinetics in Pediatric Surgery Patients

1 Month to 12 Years of Age

In general, surgical and cancer pediatric patients younger than 18 years tend to have a higher ondansetron clearance compared to adults leading to a shorter half-life in most pediatric patients. In patients 1 month to 4 months of age, a longer half-life was observed due to the higher volume of distribution in this age group.

In a study of 21 pediatric cancer patients (4 to 18 years of age) who received three intravenous doses of 0.15 mg/kg of ondansetron at 4 hour intervals, patients older than 15 years of age exhibited ondansetron pharmacokinetic parameters similar to those of adults.

Renal Impairment: Due to the very small contribution (5%) of renal clearance to the overall clearance, renal impairment was not expected to significantly influence the total clearance of ondansetron. However, ondansetron mean plasma clearance was reduced by about 41% in patients with severe renal impairment (creatinine clearance < 30 mL/min). This reduction in clearance is variable and was not consistent with an increase in half-life. No reduction in dose or dosing frequency in these patients is warranted.

Hepatic Impairment: In patients with mild-to-moderate hepatic impairment, clearance is reduced 2-fold and mean half-life is increased to 11.6 hours compared to 5.7 hours in those without hepatic impairment. In patients with severe hepatic impairment (Child-Pugh score of 10 or greater), clearance is reduced 2-fold to 3-fold and apparent volume of distribution is increased with a resultant increase in half-life to 20 hours. In patients with severe hepatic impairment, a total daily dose of 8 mg should not be exceeded.

13 NONCLINICAL TOXICOLOGY

13.1 Carcinogenesis, Mutagenesis, Impairment of Fertility

Carcinogenic effects were not seen in 2-year studies in rats and mice with oral ondansetron doses up to 10 and 30 mg/kg per day, respectively (approximately 3.6 and 5.4 times the recommended human intravenous dose of 0.15 mg/kg given three times a day, based on body surface area). Ondansetron was not mutagenic in standard tests for mutagenicity.

Oral administration of ondansetron up to 15 mg/kg per day (approximately 3.8 times the recommended human intravenous dose, based on body surface area) did not affect fertility or general reproductive performance of male and female rats.

14 CLINICAL STUDIES

The clinical efficacy of ondansetron hydrochloride, the active ingredient of ondansetron, was assessed in clinical trials as described below.

14.1 Chemotherapy-Induced Nausea and Vomiting

Adults:

In a double-blind study of three different dosing regimens of ondansetron injection, 0.015 mg/kg, 0.15 mg/kg, and 0.3 mg/kg, each given three times during the course of cancer chemotherapy, the 0.15 mg/kg dosing regimen was more effective than the 0.015 mg/kg dosing regimen. The 0.3 mg/kg dosing regimen was not shown to be more effective than the 0.15 mg/kg dosing regimen.

Cisplatin-Based Chemotherapy:

In a double-blind study in 28 patients, ondansetron injection (three 0.15 mg/kg doses) was significantly more effective than placebo in preventing nausea and vomiting induced by cisplatin-based chemotherapy. Therapeutic response was as shown in Table 6.

Table 6: Theraputic Response in Prevention of Chemotherapy-Induced

Nausea and Vomiting in Single-Day Cisplatin Therapya in Adults

a Chemotherapy was high dose (100 and 120 mg/m2; ondansetron injection n = 6, placebo n = 5) or moderate dose (50 and 80 mg/m2; ondansetron injection n = 8, placebo n = 9). Other chemotherapeutic agents included fluorouracil, doxorubicin, and cyclophosphamide. There was no difference between treatments in the types of chemotherapy that would account for differences in response.

b Efficacy based on “all patients treated” analysis.

c Median undefined since at least 50% of the patients were rescued or had more than five emetic episodes.

d Visual analog scale assessment of nausea: 0 = no nausea, 100 = nausea as bad as it can be.

e Visual analog scale assessment of satisfaction: 0 = not at all satisfied, 100 = totally satisfied.

Ondansetron injection (0.15 mg/kg x 3 doses) was compared with metoclopramide (2 mg/kg x 6 doses) in a single-blind trial in 307 patients receiving cisplatin ≥ 100 mg/m2 with or without other chemotherapeutic agents. Patients received the first dose of ondansetron or metoclopramide 30 minutes before cisplatin. Two additional ondansetron doses were administered 4 and 8 hours later, or five additional metoclopramide doses were administered 2, 4, 7, 10, and 13 hours later. Cisplatin was administered over a period of 3 hours or less. Episodes of vomiting and retching were tabulated over the period of 24 hours after cisplatin. The results of this study are summarized in Table 7.

Table 7: Therapeutic Response in Prevention of Vomiting Induced by

Cisplatin (≥ 100 mg/m2) Single-Day Therapya in Adults

a In addition to cisplatin, 68% of patients received other chemotherapeutic agents, including cyclophosphamide, etoposide, and fluorouracil. There was no difference between treatments in the types of chemotherapy that would account for differences in response.

b Visual analog scale assessment: 0 = not at all satisfied, 100 = totally satisfied.

Cyclophosphamide-Based Chemotherapy:

In a double-blind, placebo-controlled study of ondansetron injection (three 0.15 mg/kg doses) in 20 patients receiving cyclophosphamide (500 to 600 mg/m2) chemotherapy, ondansetron injection was significantly more effective than placebo in preventing nausea and vomiting. The results are summarized in Table 8.

Table 8: Therapeutic Response in Prevention of Chemotherapy-Induced Nausea and

Vomiting in Single-Day Cyclophosphamide Therapya in Adults

a Chemotherapy consisted of cyclophosphamide in all patients, plus other agents, including fluorouracil, doxorubicin, methotrexate, and vincristine. There was no difference between treatments in the type of chemotherapy that would account for differences in response.

b Efficacy based on “all patients treated” analysis.

c Median undefined since at least 50% of patients did not have any emetic episodes.

d Visual analog scale assessment of nausea: 0 = no nausea, 100 = nausea as bad as it can be.

e Visual analog scale assessment of satisfaction: 0 = not at all satisfied, 100 = totally satisfied.

Re-treatment:

In uncontrolled trials, 127 patients receiving cisplatin (median dose, 100 mg/m2) and ondansetron who had two or fewer emetic episodes were re-treated with ondansetron and chemotherapy, mainly cisplatin, for a total of 269 re-treatment courses (median, 2; range, 1 to 10). No emetic episodes occurred in 160 (59%), and two or fewer emetic episodes occurred in 217 (81%) re-treatment courses.

Pediatrics:

Four open-label, noncomparative (one US, three foreign) trials have been performed with 209 pediatric cancer patients 4 to 18 years of age given a variety of cisplatin or noncisplatin regimens. In the three foreign trials, the initial ondansetron injection dose ranged from 0.04 to 0.87 mg/kg for a total dose of 2.16 to 12 mg. This was followed by the oral administration of ondansetron ranging from 4 to 24 mg daily for 3 days. In the US trial, ondansetron was administered intravenously (only) in three doses of 0.15 mg/kg each for a total daily dose of 7.2 to 39 mg. In these studies, 58% of the 196 evaluable patients had a complete response (no emetic episodes) on day 1. Thus, prevention of vomiting in these pediatric patients was essentially the same as for patients older than 18 years of age.

An open-label, multicenter, noncomparative trial has been performed in 75 pediatric cancer patients 6 to 48 months of age receiving at least one moderately or highly emetogenic chemotherapeutic agent. Fifty-seven percent (57%) were females; 67% were white, 18% were American Hispanic, and 15% were black patients. Ondansetron was administered intravenously over 15 minutes in three doses of 0.15 mg/kg. The first dose was administered 30 minutes before the start of chemotherapy, the second and third doses were administered 4 and 8 hours after the first dose, respectively. Eighteen patients (25%) received routine prophylactic dexamethasone (i.e., not given as rescue). Of the 75 evaluable patients, 56% had a complete response (no emetic episodes) on day 1. Thus, prevention of vomiting in these pediatric patients was comparable to the prevention of vomiting in patients 4 years of age and older.

14.2 Prevention of Postoperative Nausea and/or Vomiting

Adults:

Adult surgical patients who received ondansetron immediately before the induction of general balanced anesthesia (barbiturate: thiopental, methohexital, or thiamylal; opioid: alfentanil or fentanyl; nitrous oxide; neuromuscular blockade: succinylcholine/curare and/or vecuronium or atracurium; and supplemental isoflurane) were evaluated in two double-blind US studies involving 554 patients. Ondansetron injection (4 mg) intravenous given over 2 to 5 minutes was significantly more effective than placebo. The results of these studies are summarized in Table 9.

Table 9: Therapeutic Response in Prevention of Postoperative Nausea and Vomiting in Adult Patients

The study populations in Table 9 consisted mainly of females undergoing laparoscopic procedures.

In a placebo-controlled study conducted in 468 males undergoing outpatient procedures, a single 4 mg intravenous ondansetron dose prevented postoperative vomiting over a 24-hour study period in 79% of males receiving drug compared to 63% of males receiving placebo (P <0.001).

Two other placebo-controlled studies were conducted in 2,792 patients undergoing major abdominal or gynecological surgeries to evaluate a single 4 mg or 8 mg intravenous ondansetron dose for prevention of postoperative nausea and vomiting over a 24-hour study period. At the 4 mg dosage, 59% of patients receiving ondansetron versus 45% receiving placebo in the first study (P<0.001) and 41% of patients receiving ondansetron versus 30% receiving placebo in the second study (P=0.001) experienced no emetic episodes. No additional benefit was observed in patients who received intravenous ondansetron 8 mg compared to patients who received intravenous ondansetron 4 mg.

Pediatrics:

Three double-blind, placebo-controlled studies have been performed (one US, two foreign) in 1,049 male and female patients (2 to 12 years of age) undergoing general anesthesia with nitrous oxide. The surgical procedures included tonsillectomy with or without adenoidectomy, strabismus surgery, herniorrhaphy, and orchidopexy. Patients were randomized to either single intravenous doses of ondansetron (0.1 mg/kg for pediatric patients weighing 40 kg or less, 4 mg for pediatric patients weighing more than 40 kg) or placebo. Study drug was administered over at least 30 seconds, immediately prior to or following anesthesia induction. Ondansetron was significantly more effective than placebo in preventing nausea and vomiting.

The results of these studies are summarized in Table 10.

Table 10: Therapeutic Response in Prevention of Postoperative Nausea

and Vomiting in Pediatric Patients 2 to 12 Years of Age

a Failure was one or more emetic episodes, rescued, or withdrawn.

b Nausea measured as none, mild, or severe.

A double-blind, multicenter, placebo-controlled study was conducted in 670 pediatric patients 1 month to 24 months of age who were undergoing routine surgery under general anesthesia. Seventy-five percent (75%) were males; 64% were white, 15% were black, 13% were American Hispanic, 2% were Asian, and 6% were “other race” patients. A single 0.1 mg/kg intravenous dose of ondansetron administered within 5 minutes following induction of anesthesia was statistically significantly more effective than placebo in preventing vomiting. In the placebo group, 28% of patients experienced vomiting compared to 11% of subjects who received ondansetron (P ≤ 0.01). Overall, 32 (10%) of placebo patients and 18 (5%) of patients who received ondansetron received antiemetic rescue medication(s) or prematurely withdrew from the study.

14.3 Prevention of Further Postoperative Nausea and Vomiting

Adults:

Adult surgical patients receiving general balanced anesthesia (barbiturate: thiopental, methohexital, or thiamylal; opioid: alfentanil or fentanyl; nitrous oxide; neuromuscular blockade: succinylcholine/curare and/or vecuronium or atracurium; and supplemental isoflurane) who received no prophylactic antiemetics and who experienced nausea and/or vomiting within 2 hours postoperatively were evaluated in two double-blind US studies involving 441 patients. Patients who experienced an episode of postoperative nausea and/or vomiting were given ondansetron injection (4 mg) intravenous over 2 to 5 minutes, and this was significantly more effective than placebo. The results of these studies are summarized in Table 11.

Table 11: Therapeutic Response in Prevention of Further Postoperative

Nausea and Vomiting in Adult Patients

a After administration of study drug.

b Nausea measured on a scale of 0 to 10 with 0 = no nausea, 10 = nausea as bad as it can be.

The study populations in Table 11 consisted mainly of women undergoing laparoscopic procedures.

Repeat Dosing in Adults:

In patients who do not achieve adequate control of postoperative nausea and vomiting following a single, prophylactic, preinduction, intravenous dose of ondansetron 4 mg, administration of a second intravenous dose of ondansetron 4 mg postoperatively does not provide additional control of nausea and vomiting.

Pediatrics:

One double-blind, placebo-controlled, US study was performed in 351 male and female outpatients (2 to 12 years of age) who received general anesthesia with nitrous oxide and no prophylactic antiemetics. Surgical procedures were unrestricted. Patients who experienced two or more emetic episodes within 2 hours following discontinuation of nitrous oxide were randomized to either single intravenous doses of ondansetron (0.1 mg/kg for pediatric patients weighing 40 kg or less, 4 mg for pediatric patients weighing more than 40 kg) or placebo administered over at least 30 seconds. Ondansetron was significantly more effective than placebo in preventing further episodes of nausea and vomiting. The results of the study are summarized in Table 12.

Table 12: Therapeutic Response in Prevention

of Further Postoperative Nausea and Vomiting

in Pediatric Patients 2 to 12 Years of Age

a Failure was one or more emetic episodes, rescued, or withdrawn.

16 HOW SUPPLIED/STORAGE AND HANDLING

ONDANSETRON INJECTION, USP is supplied in the following dosage forms.
NDC 51662-1366-1
ONDANSETRON INJECTION, USP 4 mg/2 mL (2 mg/mL) 2 mL VIAL

HF Acquisition Co LLC, DBA HealthFirst
Mukilteo, WA 98275

Also supplied in the following manufacture supplied dosage forms

Ondansetron Injection, USP, available as a single use (preservative free) vial, is supplied as follows:

Ondansetron Injection, USP, available as a multiple dose (preserved) vial, is supplied as follows:

Store at 2° to 25°C (36° to 77°F). Protect from light.

The container closure is not made with natural rubber latex.

17 PATIENT COUNSELING INFORMATION

Patients should be informed that ondansetron may cause serious cardiac arrhythmias such as QT prolongation. Patients should be instructed to tell their healthcare provider right away if they perceive a change in their heart rate, if they feel lightheaded, or if they have a syncopal episode.

Patients should be informed that the chances of developing severe cardiac arrhythmias such as QT prolongation and Torsades de Pointes are higher in the following people:

Patients with a personal or family history of abnormal heart rhythms, such as congenital long QT syndrome;
Patients who take medications, such as diuretics, which may cause electrolyte abnormalities
Patients with hypokalemia or hypomagnesemia

Ondansetron should be avoided in these patients, since they may be more at risk for cardiac arrhythmias such as QT prolongation and Torsades de Pointes.

Advise patients of the possibility of serotonin syndrome with concomitant use of ondansetron and another serotonergic agent such as medications to treat depression and migraines. Advise patients to seek immediate medical attention if the following symptoms occur: changes in mental status, autonomic instability, neuromuscular symptoms with or without gastrointestinal symptoms.
Inform patients that ondansetron may cause hypersensitivity reactions, some as severe as anaphylaxis and bronchospasm. The patient should report any signs and symptoms of hypersensitivity reactions, including fever, chills, rash, or breathing problems.
The patient should report the use of all medications, especially apomorphine, to their healthcare provider. Concomitant use of apomorphine and ondansetron may cause a significant drop in blood pressure and loss of consciousness.
Inform patients that ondansetron may cause headache, drowsiness/sedation, constipation, fever and diarrhea.

Lake Zurich, IL 60047
www.fresenius-kabi.us
451002G

Revised: August 2015